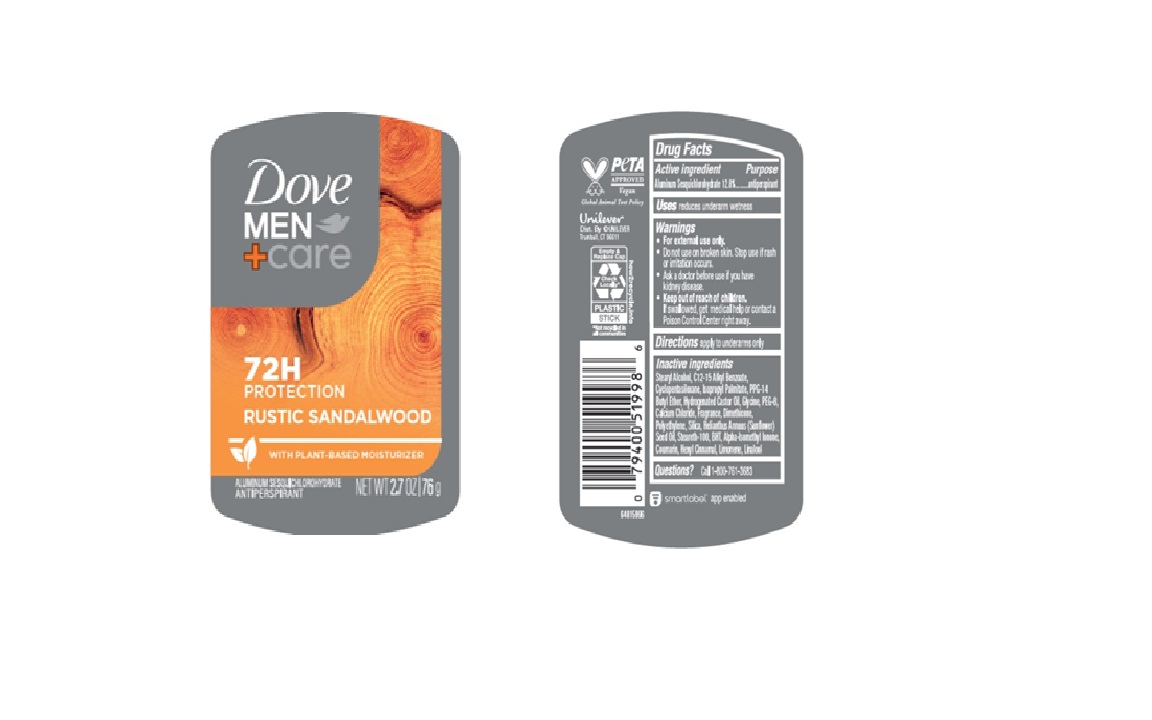 DRUG LABEL: Dove
NDC: 64942-2363 | Form: STICK
Manufacturer: Conopco d/b/a/ Unilever
Category: otc | Type: HUMAN OTC DRUG LABEL
Date: 20250331

ACTIVE INGREDIENTS: ALUMINUM SESQUICHLOROHYDRATE 12.8 g/100 g
INACTIVE INGREDIENTS: STEARYL ALCOHOL; HYDROGENATED CASTOR OIL; CALCIUM CHLORIDE; COUMARIN; HELIANTHUS ANNUUS (SUNFLOWER) SEED OIL; DIMETHICONE; SILICA; STEARETH-100; C12-15 ALKYL BENZOATE; ISOPROPYL PALMITATE; PEG-8; POLYETHYLENE; ALPHA-ISOMETHYL IONONE; HEXYL CINNAMAL; LIMONENE, (+)-; LINALOOL, (+/-)-; PPG-14 BUTYL ETHER; CYCLOPENTASILOXANE; BHT; GLYCINE

Dove Men + Care Rustic Sandalwood 72H Antiperspirant

DESCRIPTION

Dove Men + Care Rustic Sandalwood 72H Antiperspirant

ACTIVE INGREDIENT

Aluminum Sesquichlorohydrate (12.8%)

PURPOSE

Antiperspirant

INDICATIONS AND USAGE

reduces underarm wetness

WARNINGS

For external use only.

Do not use on broken skin.

Stop use if rash or irritation occurs.

Ask a doctor before use if you have kidney disease.

Keep out of reach of children. If swallowed, get medical help or contact a Poison Control Center right away.

DOSAGE AND ADMINISTRATION

Apply to underarms only

INACTIVE INGREDIENT

Stearyl Alcohol, C12-15 Alkyl Benzoate, Cyclopentasiloxane, Isopropyl Palmitate, PPG-14 Butyl Ether, Hydrogenated Castor Oil, Glycine, PEG-8, Calcium Chloride, Fragrance, Dimethicone, Polyethylene, Silica, Helianthus Annuus (Sunflower) Seed Oil, Steareth-100, BHT, Alpha-Isomethyl Ionone, Coumarin, Hexyl Cinnamal, Limonene, Linalool

QUESTIONS

Call 1-800-761-3683